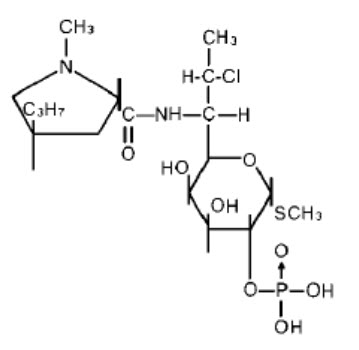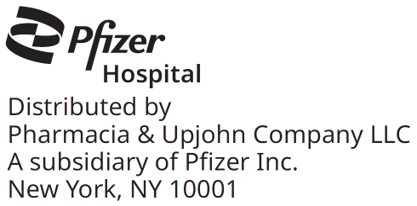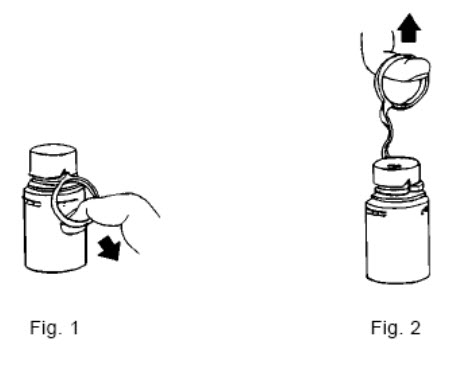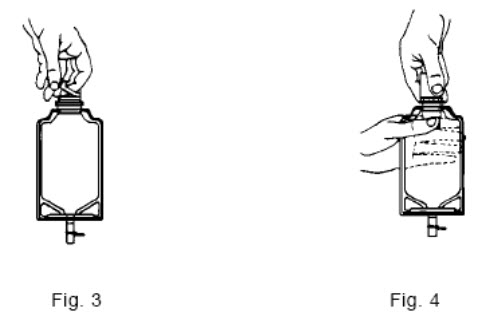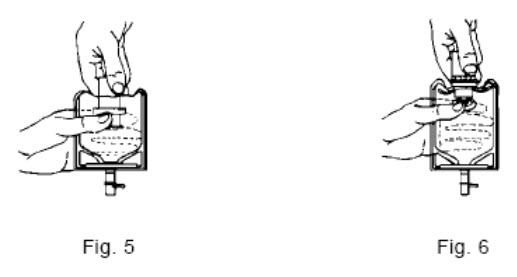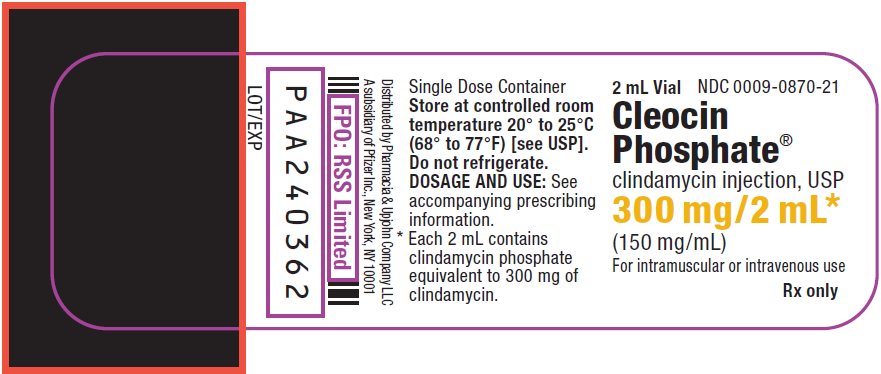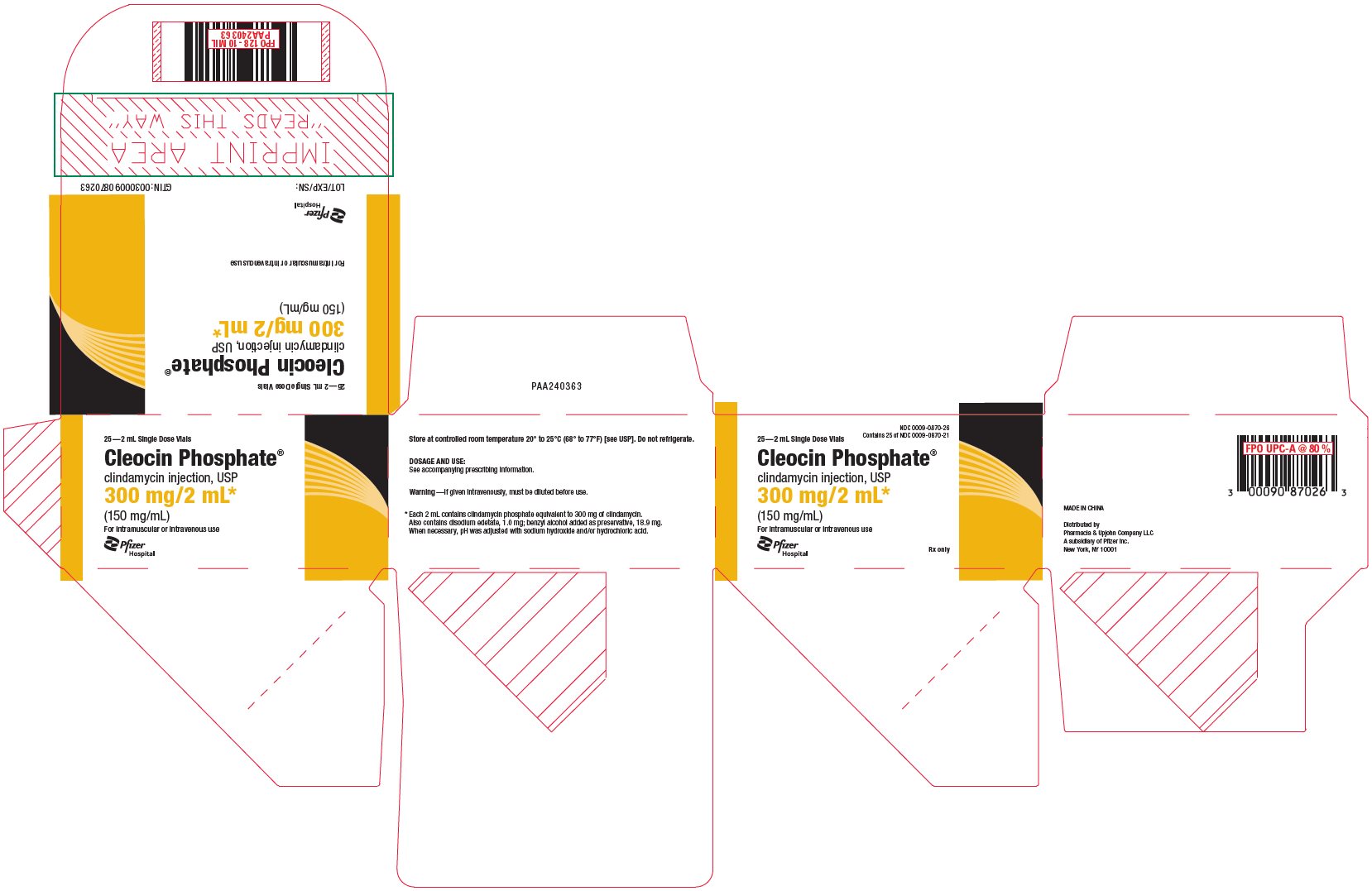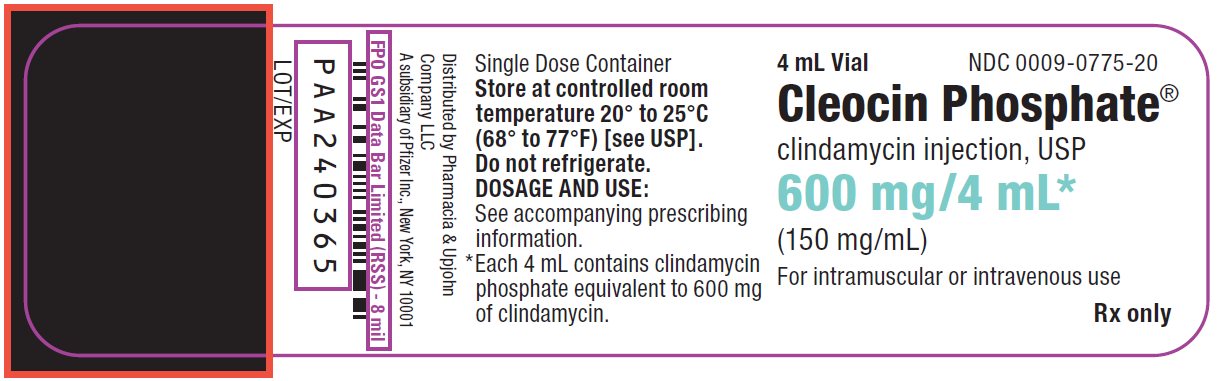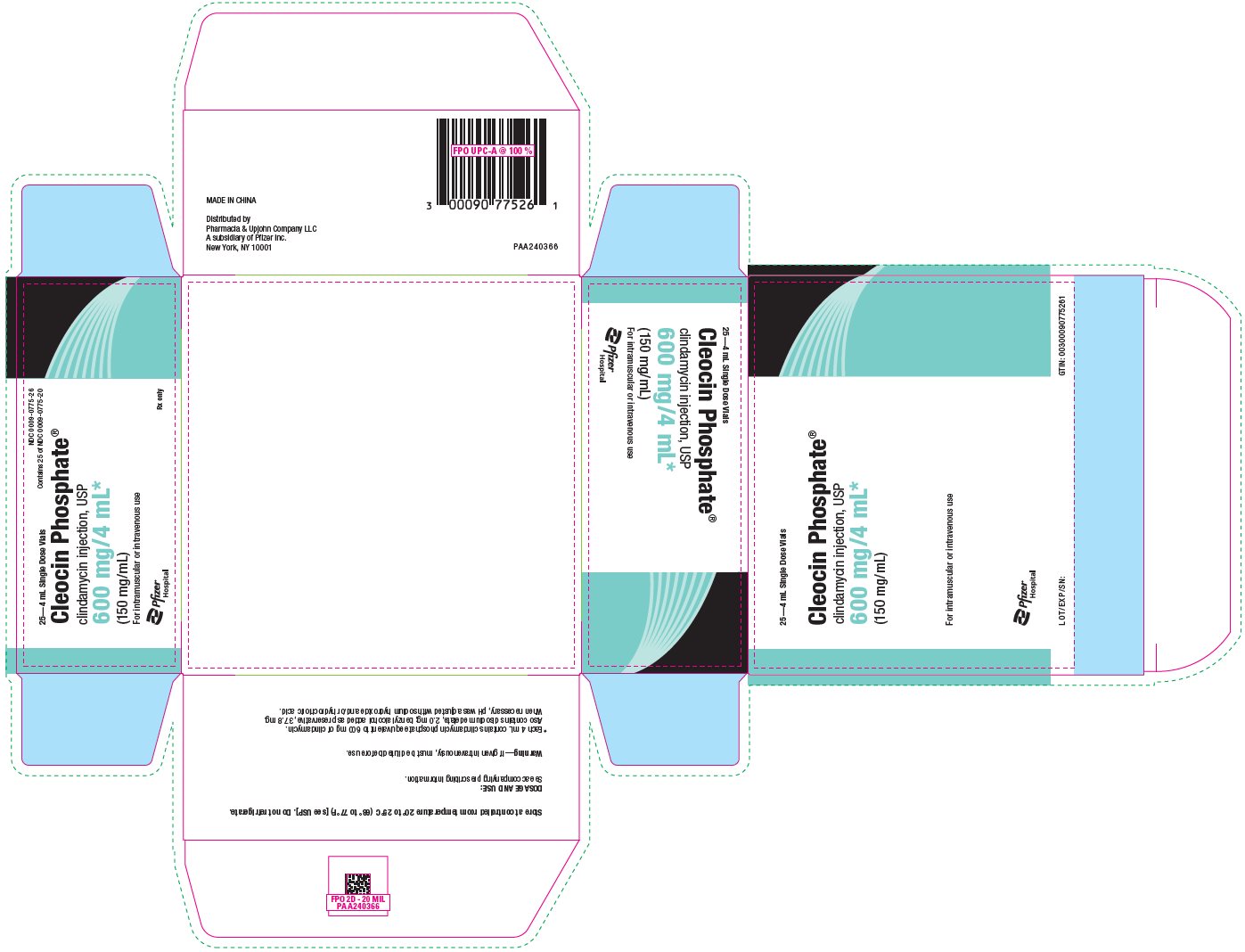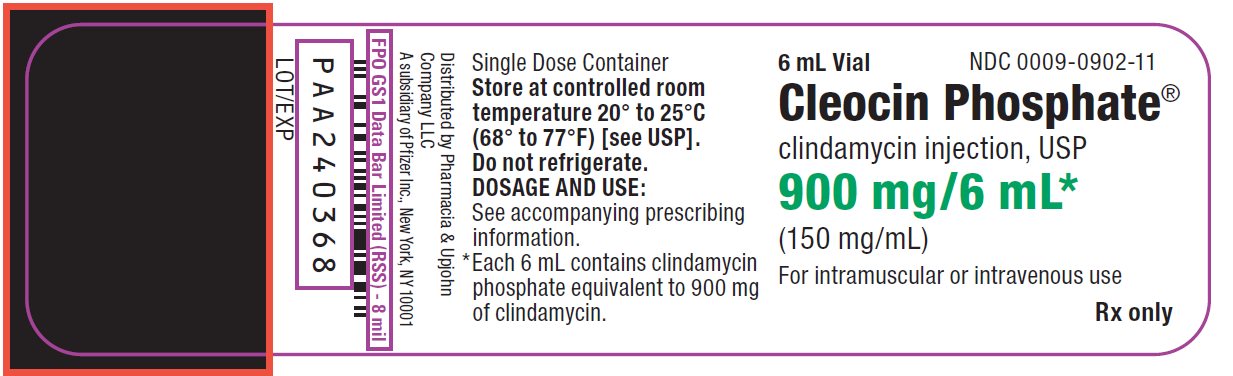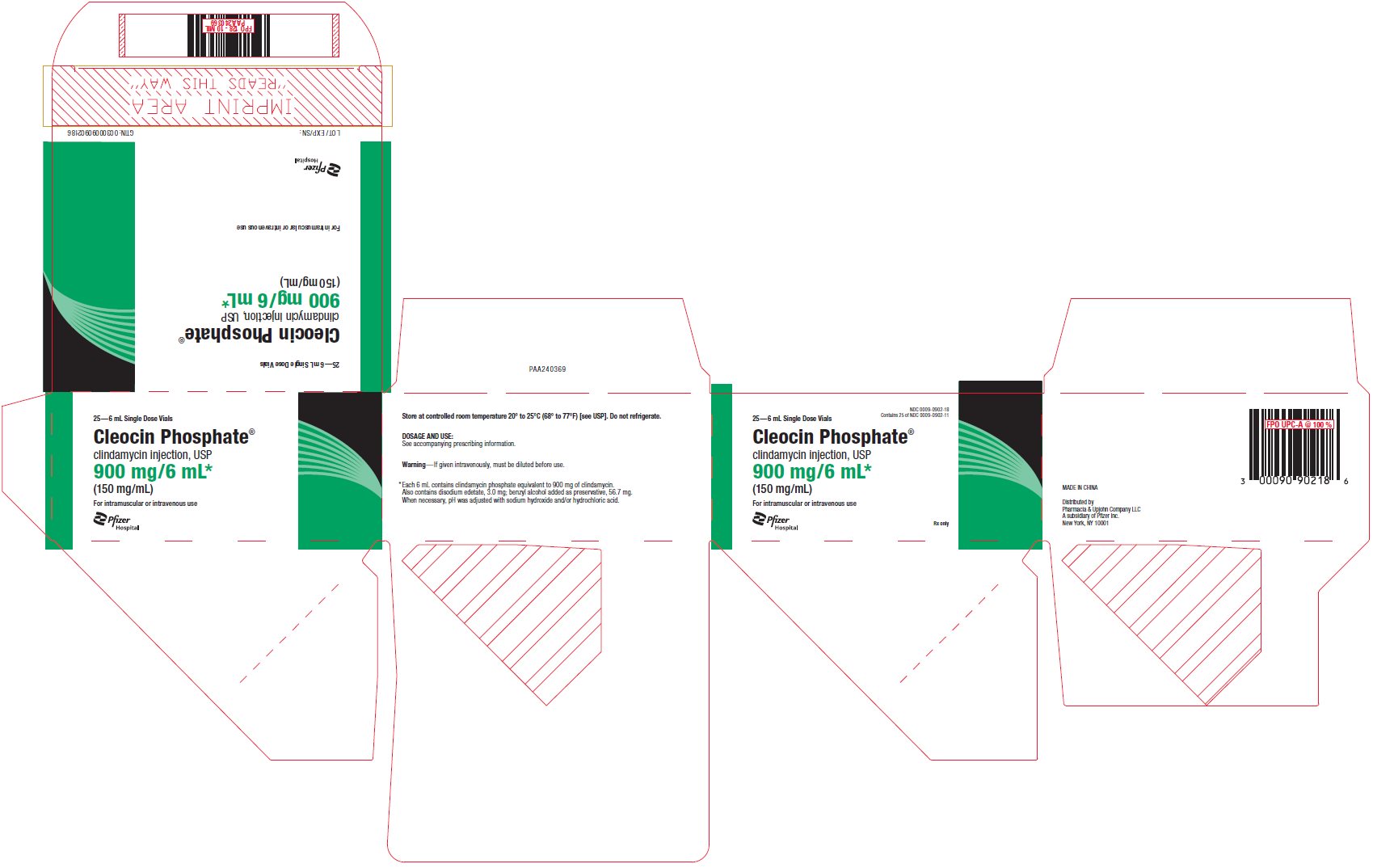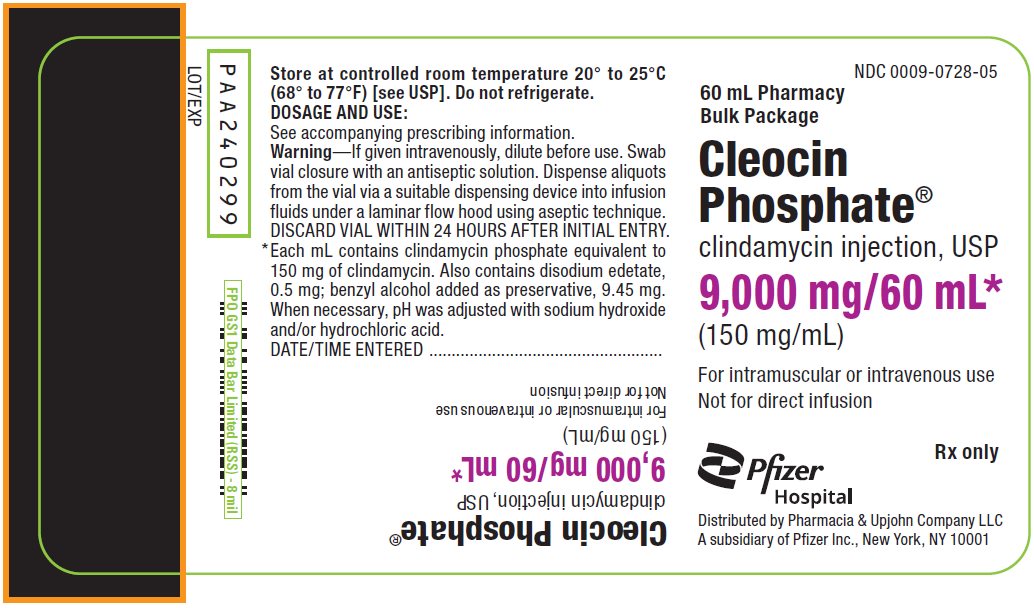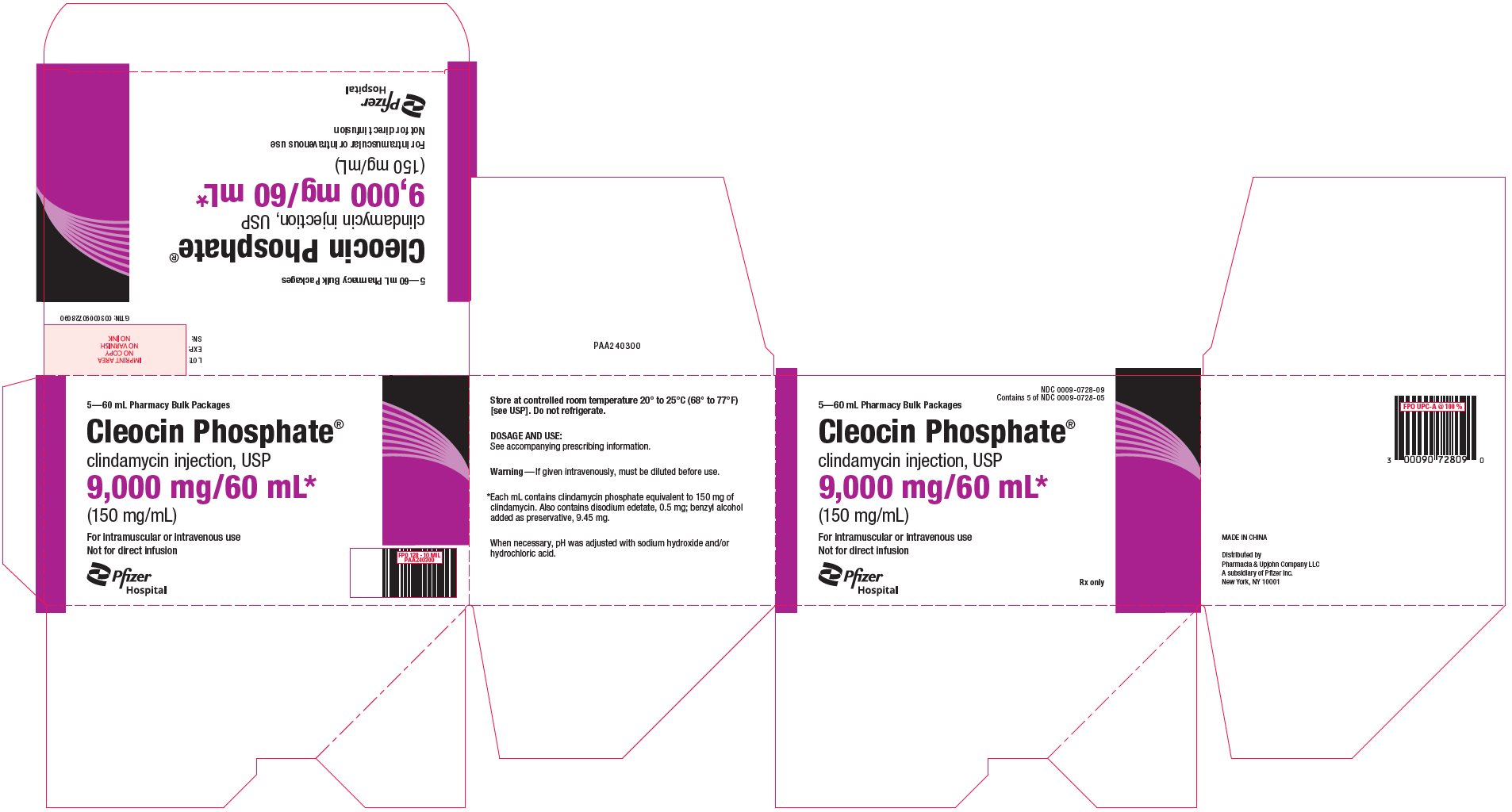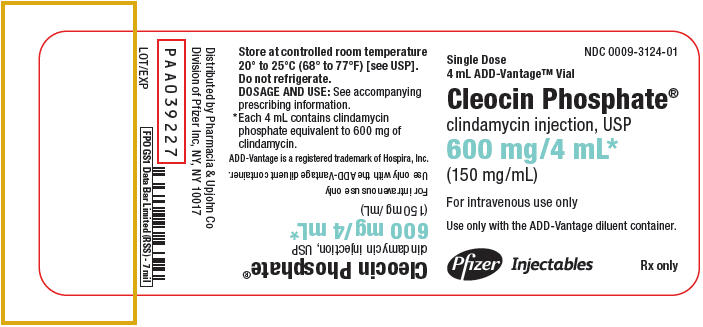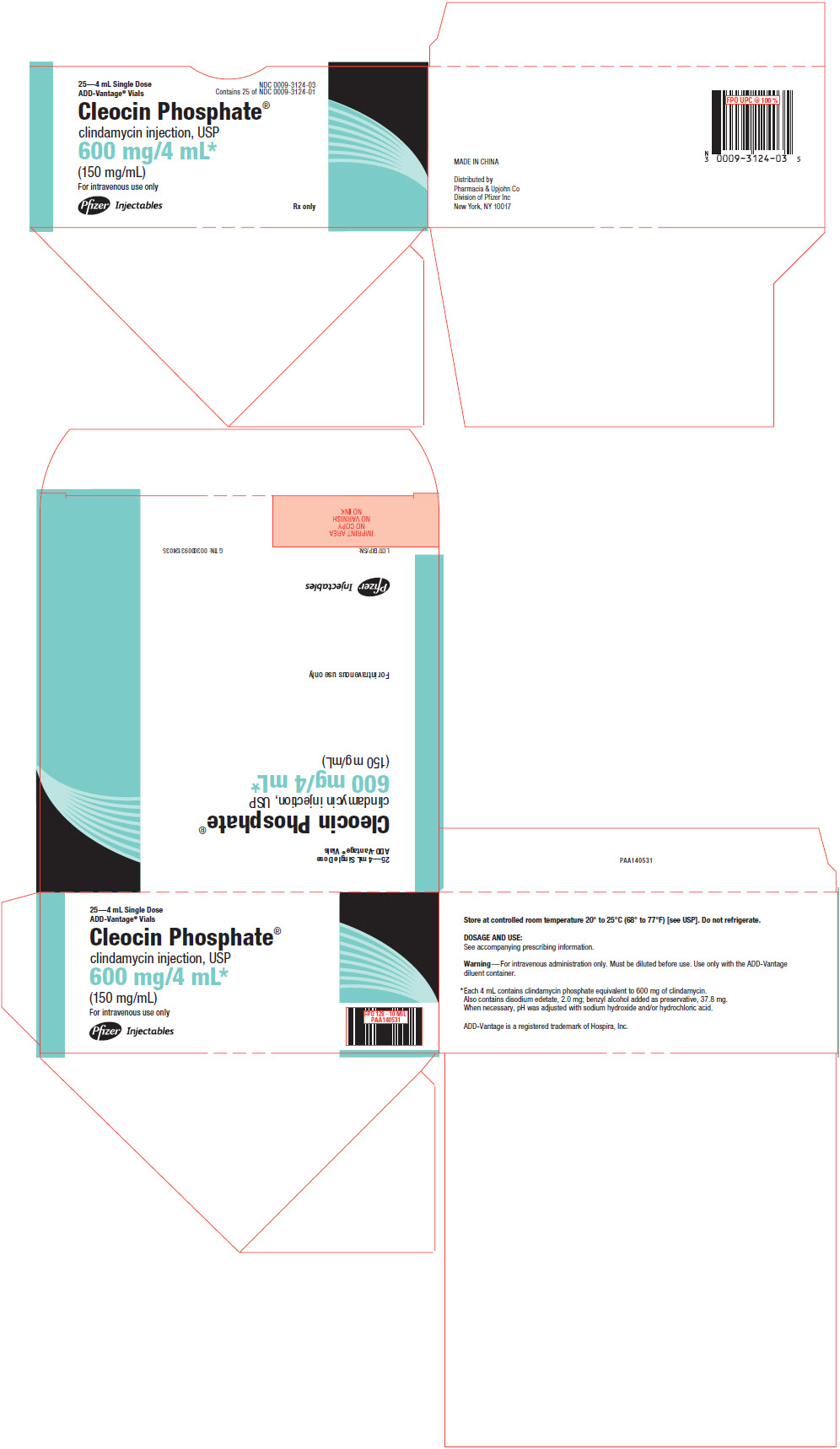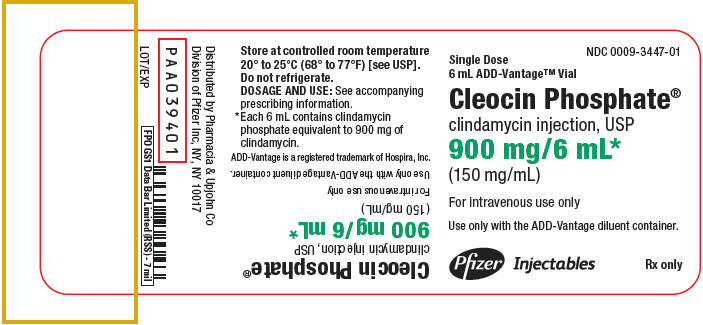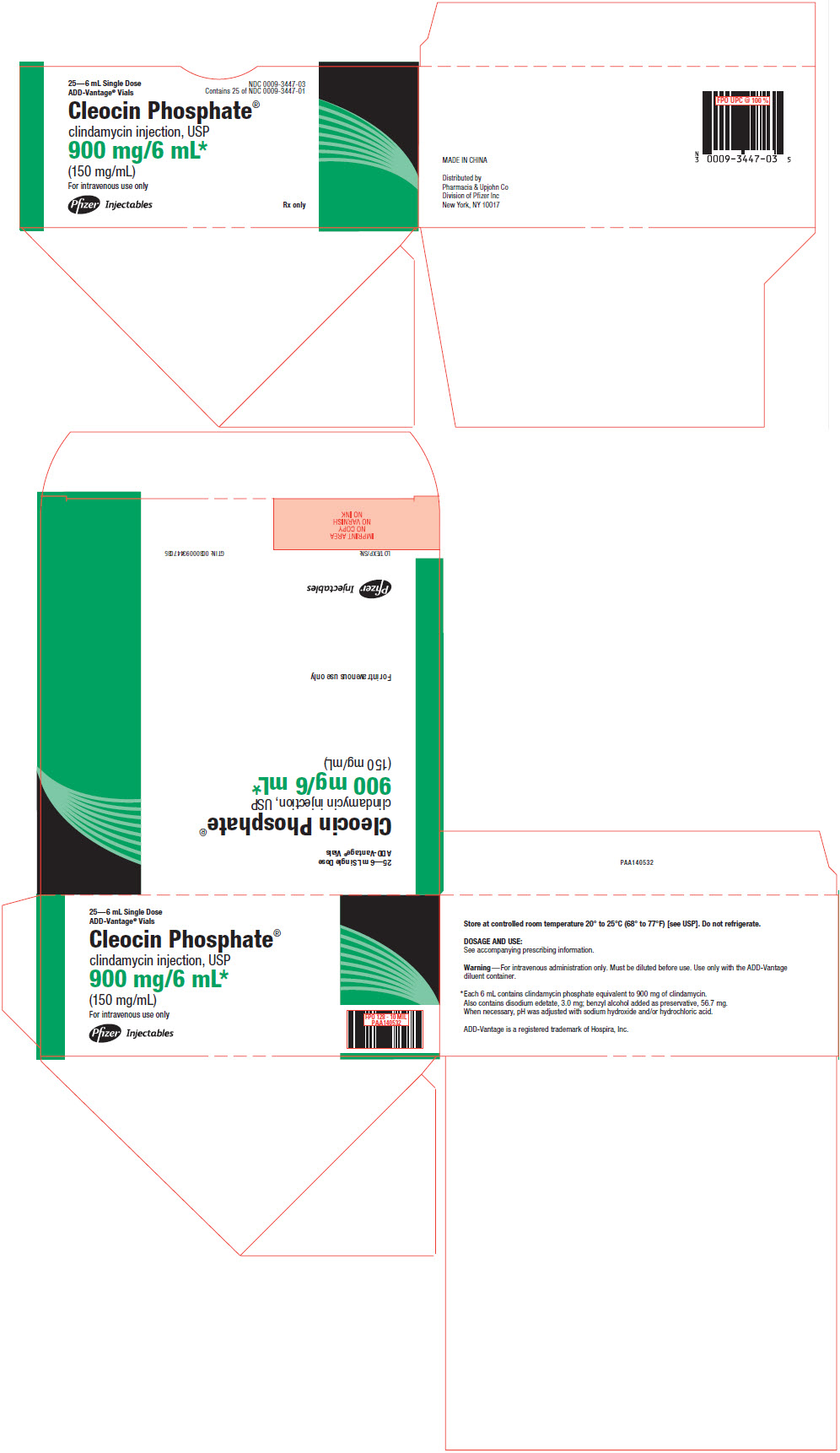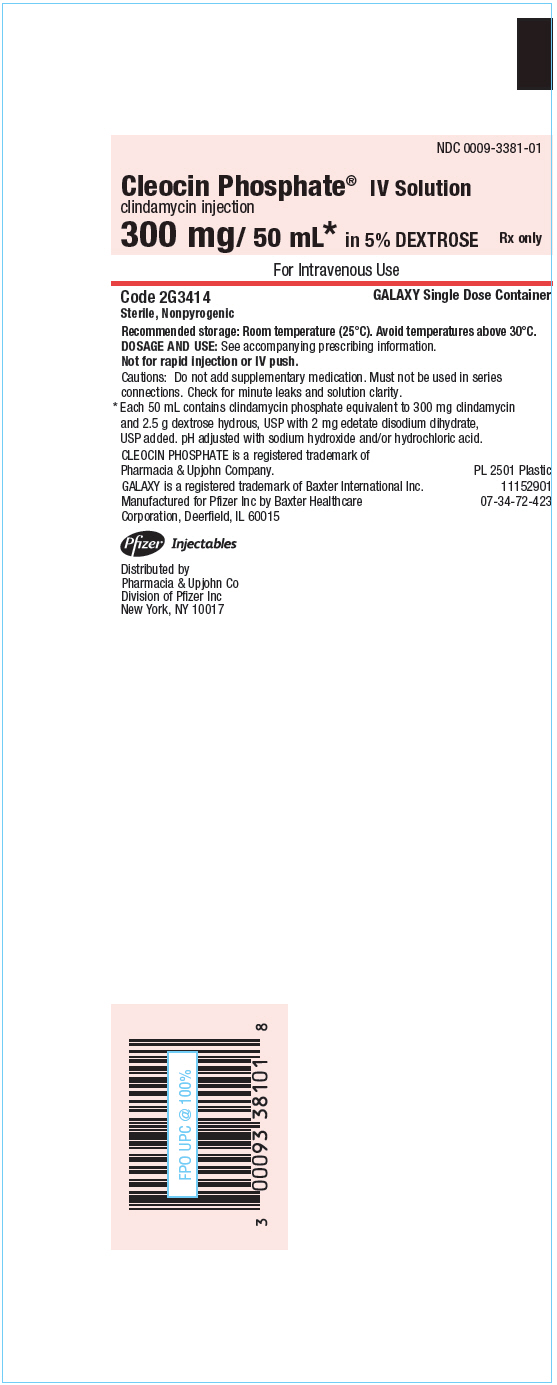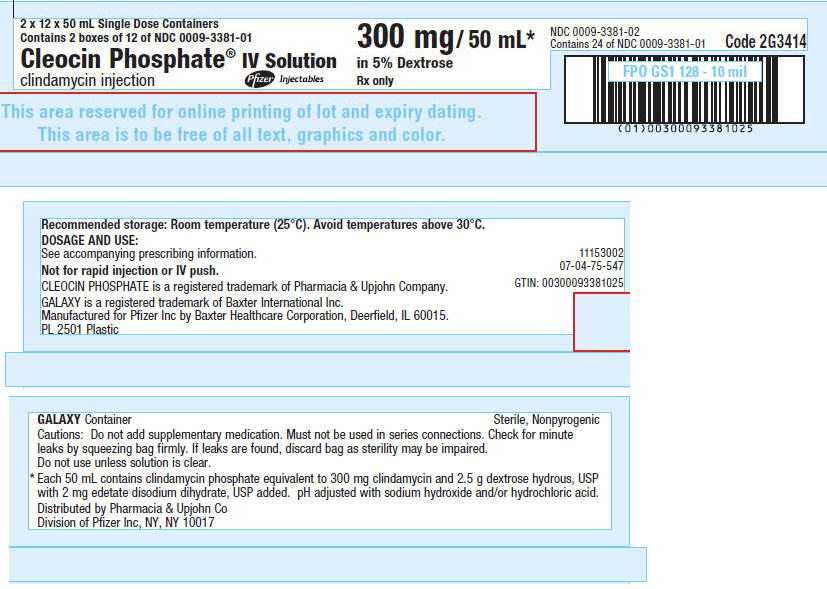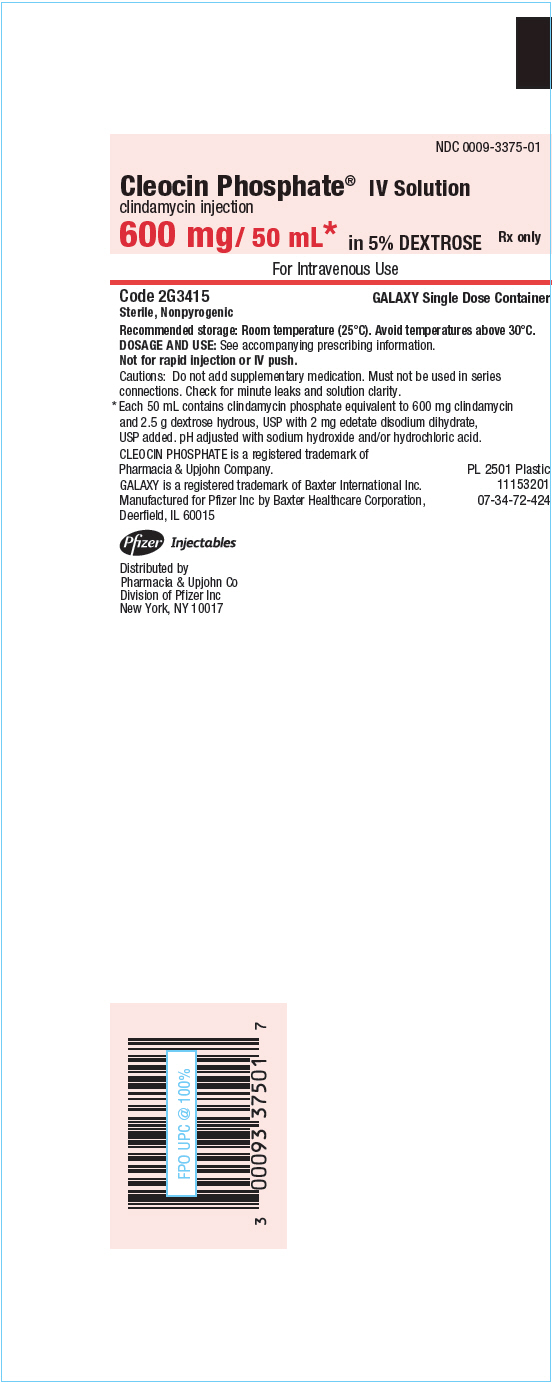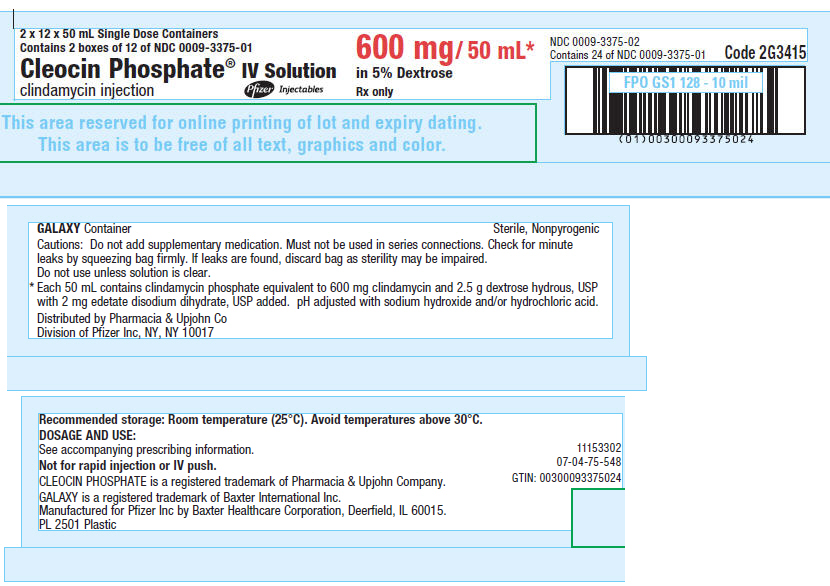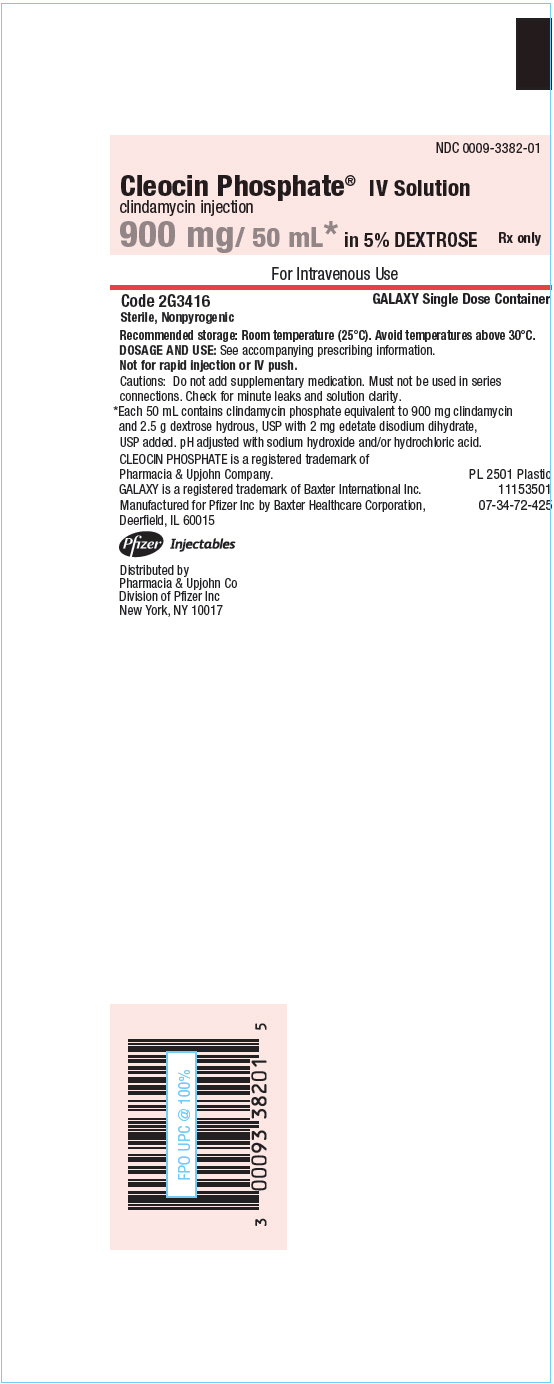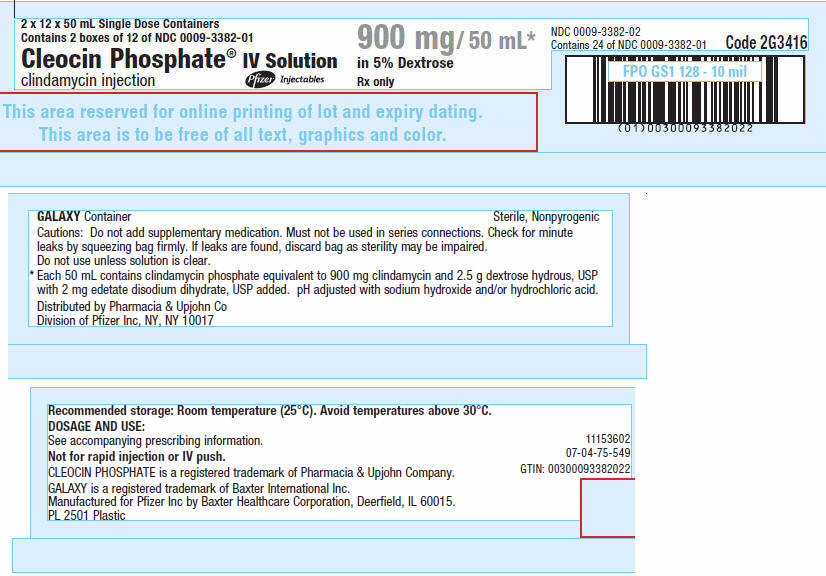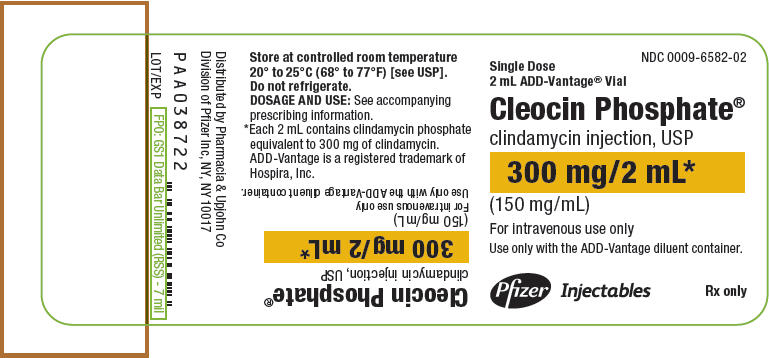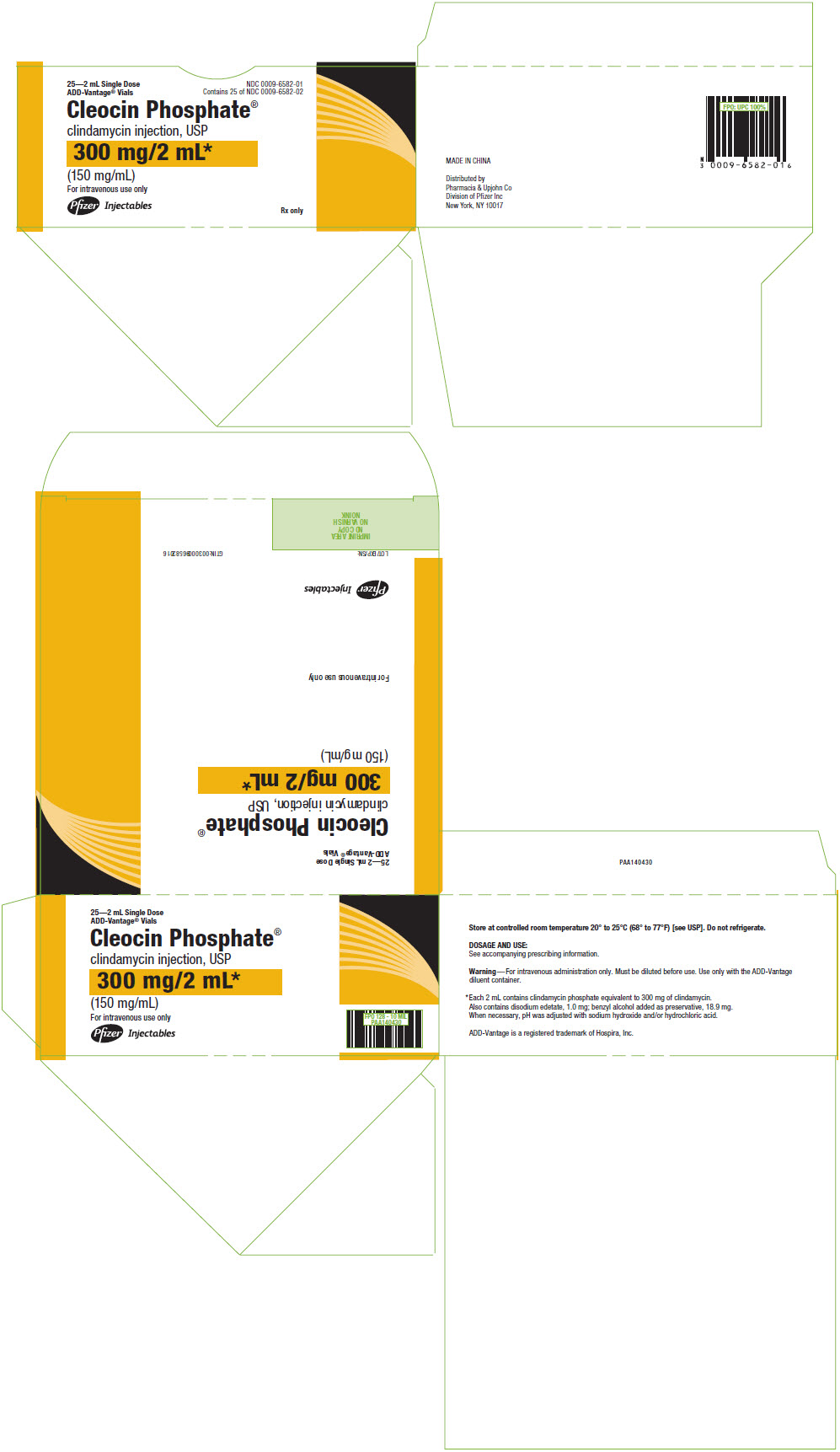 DRUG LABEL: Cleocin Phosphate
NDC: 0009-0870 | Form: INJECTION, SOLUTION
Manufacturer: Pharmacia & Upjohn Company LLC
Category: prescription | Type: HUMAN PRESCRIPTION DRUG LABEL
Date: 20251120

ACTIVE INGREDIENTS: CLINDAMYCIN PHOSPHATE 150 mg/1 mL

CLEOCIN PHOSPHATE®
(clindamycin injection, USP) and
(clindamycin injection in 5% dextrose)

To reduce the development of drug-resistant bacteria and maintain the effectiveness of CLEOCIN PHOSPHATE and other antibacterial drugs, CLEOCIN PHOSPHATE should be used only to treat or prevent infections that are proven or strongly suspected to be caused by bacteria.

Sterile Solution is for Intramuscular and Intravenous Use

CLEOCIN PHOSPHATE in the ADD-Vantage® Vial is For Intravenous Use Only

WARNING

Clostridioides difficile-associated diarrhea (CDAD) has been reported with use of nearly all antibacterial agents, including CLEOCIN PHOSPHATE and may range in severity from mild diarrhea to fatal colitis. Treatment with antibacterial agents alters the normal flora of the colon leading to overgrowth of C. difficile.

Because CLEOCIN PHOSPHATE therapy has been associated with severe colitis which may end fatally, it should be reserved for serious infections where less toxic antimicrobial agents are inappropriate, as described in the INDICATIONS AND USAGE section. It should not be used in patients with nonbacterial infections such as most upper respiratory tract infections.

C. difficile produces toxins A and B which contribute to the development of CDAD. Hypertoxin producing strains of C. difficile cause increased morbidity and mortality, as these infections can be refractory to antimicrobial therapy and may require colectomy. CDAD must be considered in all patients who present with diarrhea following antibacterial drug use. Careful medical history is necessary since CDAD has been reported to occur over two months after the administration of antibacterial agents.

If CDAD is suspected or confirmed, ongoing antibacterial drug use not directed against C. difficile may need to be discontinued. Appropriate fluid and electrolyte management, protein supplementation, antibacterial drug treatment of C. difficile, and surgical evaluation should be instituted as clinically indicated.

DESCRIPTION

CLEOCIN PHOSPHATE Sterile Solution in vials contains clindamycin phosphate, a water soluble ester of clindamycin and phosphoric acid. Each mL contains the equivalent of 150 mg clindamycin, 0.5 mg disodium edetate and 9.45 mg benzyl alcohol added as preservative in each mL. Clindamycin is a semisynthetic antibacterial drug produced by a 7(S)-chloro-substitution of the 7(R)-hydroxyl group of the parent compound lincomycin.

The chemical name of clindamycin phosphate is L-threo-α-D-galacto-Octopyranoside, methyl-7-chloro-6,7,8-trideoxy-6-[[(1-methyl-4-propyl-2-pyrrolidinyl)carbonyl] amino]-1-thio-, 2-(dihydrogen phosphate), (2S-trans)-.

The molecular formula is C18H34ClN2O8PS and the molecular weight is 504.96.

The structural formula is represented below:

CLEOCIN PHOSPHATE in the ADD-Vantage Vial is intended for intravenous use only after further dilution with appropriate volume of ADD-Vantage diluent base solution (see Directions for Use).

CLEOCIN PHOSPHATE IV Solution in the GALAXY plastic container for intravenous use is composed of clindamycin phosphate equivalent to 300, 600 and 900 mg of clindamycin premixed with 5% dextrose as a sterile solution. Disodium edetate has been added at a concentration of 0.04 mg/mL. The pH has been adjusted with sodium hydroxide and/or hydrochloric acid.

The plastic container is fabricated from a specially designed multilayer plastic, PL 2501. Solutions in contact with the plastic container can leach out certain of its chemical components in very small amounts within the expiration period. The suitability of the plastic has been confirmed in tests in animals according to the USP biological tests for plastic containers, as well as by tissue culture toxicity studies.

CLINICAL PHARMACOLOGY

Distribution

Biologically inactive clindamycin phosphate is converted to active clindamycin. By the end of short-term intravenous infusion, peak serum concentrations of active clindamycin are reached.

After intramuscular injection of clindamycin phosphate, peak concentrations of active clindamycin are reached within 3 hours in adults and 1 hour in pediatric patients.

Serum concentrations of clindamycin can be maintained above the in vitro minimum inhibitory concentrations for most indicated organisms by administration of clindamycin phosphate every 8 to 12 hours in adults and every 6 to 8 hours in pediatric patients, or by continuous intravenous infusion. An equilibrium state is reached by the third dose.

No significant concentrations of clindamycin are attained in the cerebrospinal fluid even in the presence of inflamed meninges.

Metabolism

In vitro studies in human liver and intestinal microsomes indicated that clindamycin is predominantly metabolized by Cytochrome P450 3A4 (CYP3A4), with minor contribution from CYP3A5, to form clindamycin sulfoxide and a minor metabolite, N-desmethylclindamycin.

Excretion

Biologically inactive clindamycin phosphate disappears from the serum with 6 minutes of the average elimination half-life; however, the average serum elimination half-life of active clindamycin is about 3 hours in adults and 2½ hours in pediatric patients.

Specific Populations

Patients with Renal/Hepatic Impairment

The elimination half-life of clindamycin is increased slightly in patients with markedly reduced renal or hepatic function. Hemodialysis and peritoneal dialysis are not effective in removing clindamycin from the serum. Dosage schedules do not need to be modified in patients with renal or hepatic disease.

Geriatric Patients

Pharmacokinetic studies in elderly volunteers (61–79 years) and younger adults (18–39 years) indicate that age alone does not alter clindamycin pharmacokinetics (clearance, elimination half-life, volume of distribution, and area under the serum concentration-time curve) after IV administration of clindamycin phosphate. After oral administration of clindamycin hydrochloride, the average elimination half-life is increased to approximately 4.0 hours (range 3.4–5.1 h) in the elderly, compared to 3.2 hours (range 2.1–4.2 h) in younger adults. The extent of absorption, however, is not different between age groups and no dosage alteration is necessary for the elderly with normal hepatic function and normal (age-adjusted) renal function^1.

Pharmacokinetics in Pediatric Patients with PMA ≤32 weeks, or >32 to ≤40 weeks

Systemic clearance (CL) in premature infants increases with increases in body weight (kg) and post-menstrual age (PMA). The dosing regimens for pediatric patients ≤32 weeks PMA (5 mg/kg) and >32 to ≤40 weeks PMA (7 mg/kg), both administered intravenously every 8 hours, achieve exposures comparable to therapeutic exposures in adults (weighing 70 kg) administered clindamycin 600 mg every 8 hours (Table 1).

Table 1: Predicted Drug Exposure (Mean ± SD) of Clindamycin in Adults and in Pediatric Patients with PMA ≤32 weeks, or >32 to ≤40 weeks
Age | Adult (70 kg) | PMA ≤32 weeks | PMA>32 – ≤40 weeks
Dose (every 8 hours) | 600 mg | 5 mg/kg | 7 mg/kg
AUCss,0–8 hour (mcg∙h/mL) | 50.5 (30.95) | 52.5 (17.0) | 55.9 (23.55)
Cmax,ss (mcg/mL) | 12.0 (3.49) | 9.0 (2.02) | 10.5 (2.79)
Cmin,ss (mcg/mL) | 3.1 (3.34) | 4.6 (2.00) | 4.4 (2.77)
PMA: post-menstrual age; AUCss,0–8 hour: area under the concentration-time curve during a dosing interval at steady state; Cmax,ss: maximum drug concentration at steady state; Cmin,ss: minimum or trough drug concentration at steady state.

Obese Pediatric Patients Aged 2 to Less than 18 Years and Obese Adults Aged 18 to 20 Years

An analysis of pharmacokinetic data in obese pediatric patients aged 2 to less than 18 years and obese adults aged 18 to 20 years demonstrated that clindamycin clearance and volume of distribution, normalized by total body weight, are comparable regardless of obesity.

Microbiology

Mechanism of Action

Clindamycin inhibits bacterial protein synthesis by binding to the 23S RNA of the 50S subunit of the ribosome. Clindamycin is bacteriostatic.

Resistance

Resistance to clindamycin is most often caused by modification of specific bases of the 23S ribosomal RNA. Cross-resistance between clindamycin and lincomycin is complete. Because the binding sites for these antibacterial drugs overlap, cross-resistance is sometimes observed among lincosamides, macrolides and streptogramin B.Macrolide-inducible resistance to clindamycin occurs in some isolates of macrolide-resistant bacteria. Macrolide-resistant isolates of staphylococci and beta-hemolytic streptococci should be screened for induction of clindamycin resistance using the D-zone test.

Antimicrobial Activity

Clindamycin has been shown to be active against most of the isolates of the following microorganisms, both in vitro and in clinical infections [see Indications and Usage ]:

Gram-positive bacteria

Staphylococcus aureus (methicillin-susceptible strains)
Streptococcus pneumoniae (penicillin-susceptible strains)
Streptococcus pyogenes

Anaerobic bacteria

Clostridium perfringens
Fusobacterium necrophorum
Fusobacterium nucleatum
Peptostreptococcus anaerobius
Prevotella melaninogenica

The following in vitro data are available, but their clinical significance is unknown. At least 90 percent of the following bacteria exhibit an in vitro minimum inhibitory concentration (MIC) less than or equal to the susceptible breakpoint for clindamycin against isolates of a similar genus or organism group. However, the efficacy of clindamycin in treating clinical infections due to these bacteria has not been established in adequate and well-controlled clinical trials.

Gram-positive bacteria

Staphylococcus epidermidis (methicillin-susceptible strains)
Streptococcus agalactiae
Streptococcus anginosus
Streptococcus mitis
Streptococcus oralis

Anaerobic bacteria

Actinomyces israelii
Clostridium clostridioforme
Eggerthella lenta
Finegoldia (Peptostreptococcus) magna
Micromonas (Peptostreptococcus) micros
Prevotella bivia
Prevotella intermedia
Cutibacterium acnes

Susceptibility Testing

For specific information regarding susceptibility test interpretive criteria and associated test methods and quality control standards recognized by FDA for this drug, please see: https://www.fda.gov/STIC.

INDICATIONS AND USAGE

CLEOCIN PHOSPHATE products are indicated in the treatment of serious infections caused by susceptible anaerobic bacteria.

CLEOCIN PHOSPHATE products are also indicated in the treatment of serious infections due to susceptible strains of streptococci, pneumococci, and staphylococci. Its use should be reserved for penicillin-allergic patients or other patients for whom, in the judgment of the physician, a penicillin is inappropriate. Because of the risk of antibacterial drug-associated pseudomembranous colitis, as described in the BOXED WARNING, before selecting clindamycin the physician should consider the nature of the infection and the suitability of less toxic alternatives (e.g., erythromycin).

Bacteriologic studies should be performed to determine the causative organisms and their susceptibility to clindamycin.

Indicated surgical procedures should be performed in conjunction with antibacterial drug therapy.

CLEOCIN PHOSPHATE is indicated in the treatment of serious infections caused by susceptible strains of the designated organisms in the conditions listed below:

Lower respiratory tract infections including pneumonia, empyema, and lung abscess caused by anaerobes, Streptococcus pneumoniae, other streptococci (except E. faecalis), and Staphylococcus aureus.

Skin and skin structure infections caused by Streptococcus pyogenes, Staphylococcus aureus, and anaerobes.

Gynecological infections including endometritis, nongonococcal tubo-ovarian abscess, pelvic cellulitis, and postsurgical vaginal cuff infection caused by susceptible anaerobes.

Intra-abdominal infections including peritonitis and intra-abdominal abscess caused by susceptible anaerobic organisms.

Septicemia caused by Staphylococcus aureus, streptococci (except Enterococcus faecalis), and susceptible anaerobes.

Bone and joint infections including acute hematogenous osteomyelitis caused by Staphylococcus aureus and as adjunctive therapy in the surgical treatment of chronic bone and joint infections due to susceptible organisms.

To reduce the development of drug-resistant bacteria and maintain the effectiveness of CLEOCIN PHOSPHATE and other antibacterial drugs, CLEOCIN PHOSPHATE should be used only to treat or prevent infections that are proven or strongly suspected to be caused by susceptible bacteria. When culture and susceptibility information are available, they should be considered in selecting or modifying antibacterial therapy. In the absence of such data, local epidemiology and susceptibility patterns may contribute to the empiric selection of therapy.

CONTRAINDICATIONS

This drug is contraindicated in individuals with a history of hypersensitivity to preparations containing clindamycin or lincomycin.

WARNINGS

See BOXED WARNING.

Clostridioides difficile-associated diarrhea (CDAD) has been reported with use of nearly all antibacterial agents, including CLEOCIN PHOSPHATE, and may range in severity from mild diarrhea to fatal colitis. Treatment with antibacterial agents alters the normal flora of the colon leading to overgrowth of C. difficile.

C. difficile produces toxins A and B which contribute to the development of CDAD. Hypertoxin producing strains of C. difficile cause increased morbidity and mortality, as these infections can be refractory to antimicrobial therapy and may require colectomy. CDAD must be considered in all patients who present with diarrhea following antibacterial drug use. Careful medical history is necessary since CDAD has been reported to occur over two months after the administration of antibacterial agents.

If CDAD is suspected or confirmed, ongoing antibacterial drug use not directed against C. difficile may need to be discontinued. Appropriate fluid and electrolyte management, protein supplementation, antibacterial drug treatment of C. difficile, and surgical evaluation should be instituted as clinically indicated.

Anaphylactic and Severe Hypersensitivity Reactions

Anaphylactic shock and anaphylactic reactions have been reported (see ADVERSE REACTIONS).

Severe hypersensitivity reactions, including severe skin reactions such as toxic epidermal necrolysis (TEN), drug reaction with eosinophilia and systemic symptoms (DRESS), Stevens-Johnson syndrome (SJS), and Kounis syndrome, some with fatal outcome, have been reported (see ADVERSE REACTIONS).

In case of such an anaphylactic or severe hypersensitivity reaction, discontinue treatment permanently and institute appropriate therapy.

A careful inquiry should be made concerning previous sensitivities to drugs and other allergens.

Benzyl Alcohol Toxicity in Neonates ("Gasping Syndrome")

This product contains benzyl alcohol as a preservative. The administration of intravenous solutions containing the preservative benzyl alcohol has been associated with the "gasping syndrome", and death in neonates. Symptoms include a striking onset of gasping respiration, hypotension, bradycardia, and cardiovascular collapse. Although the normal therapeutic dose of this product delivers amounts of benzyl alcohol that are substantially lower than those reported in association with the "gasping syndrome", the minimum amount of benzyl alcohol at which toxicity may occur is not known and total daily benzyl alcohol exposure may be increased by concomitant medications.

The risk of benzyl alcohol toxicity depends on the quantity administered and the liver and kidneys' capacity to detoxify the chemical. Premature and low birth weight infants may be more likely to develop toxicity.

Nephrotoxicity

Clindamycin is potentially nephrotoxic and cases with acute kidney injury have been reported. Consider monitoring of renal function particularly in patients with pre-existing renal dysfunction or those taking concomitant nephrotoxic drugs. In case of acute kidney injury, discontinue CLEOCIN PHOSPHATE when no other etiology is identified.

Usage in Meningitis

Since clindamycin does not diffuse adequately into the cerebrospinal fluid, the drug should not be used in the treatment of meningitis.

PRECAUTIONS

General

Review of experience to date suggests that a subgroup of older patients with associated severe illness may tolerate diarrhea less well. When clindamycin is indicated in these patients, they should be carefully monitored for change in bowel frequency.

CLEOCIN PHOSPHATE products should be prescribed with caution in individuals with a history of gastrointestinal disease, particularly colitis.

CLEOCIN PHOSPHATE should be prescribed with caution in atopic individuals.

Certain infections may require incision and drainage or other indicated surgical procedures in addition to antibacterial drug therapy.

The use of CLEOCIN PHOSPHATE may result in overgrowth of nonsusceptible organisms-particularly yeasts. Should superinfections occur, appropriate measures should be taken as indicated by the clinical situation.

CLEOCIN PHOSPHATE should not be injected intravenously undiluted as a bolus, but should be infused over at least 10–60 minutes as directed in the DOSAGE AND ADMINISTRATION section.

Clindamycin dosage modification is not necessary in patients with renal disease. In patients with moderate to severe liver disease, prolongation of clindamycin half-life has been found. However, it was postulated from studies that when given every eight hours, accumulation should rarely occur. Therefore, dosage modification in patients with liver disease may not be necessary. However, periodic liver enzyme determinations should be made when treating patients with severe liver disease.

Prescribing CLEOCIN PHOSPHATE in the absence of a proven or strongly suspected bacterial infection or a prophylactic indication is unlikely to provide benefit to the patient and increases the risk of the development of drug-resistant bacteria.

Information for Patients

Patients should be counseled that antibacterial drugs including CLEOCIN PHOSPHATE should only be used to treat bacterial infections. They do not treat viral infections (e.g., the common cold). When CLEOCIN PHOSPHATE is prescribed to treat a bacterial infection, patients should be told that although it is common to feel better early in the course of therapy, the medication should be taken exactly as directed. Skipping doses or not completing the full course of therapy may (1) decrease the effectiveness of the immediate treatment and (2) increase the likelihood that bacteria will develop resistance and will not be treatable by CLEOCIN PHOSPHATE or other antibacterial drugs in the future.

Diarrhea is a common problem caused by antibacterial drugs which usually ends when the antibacterial drug is discontinued. Sometimes after starting treatment with antibacterial drugs, patients can develop watery and bloody stools (with or without stomach cramps and fever) even as late as two or more months after having taken the last dose of the antibacterial drug. If this occurs, patients should contact their physician as soon as possible.

Laboratory Tests

During prolonged therapy periodic liver and kidney function tests and blood counts should be performed.

Drug Interactions

Clindamycin has been shown to have neuromuscular blocking properties that may enhance the action of other neuromuscular blocking agents. Therefore, it should be used with caution in patients receiving such agents.

Clindamycin is metabolized predominantly by CYP3A4, and to a lesser extent by CYP3A5, to the major metabolite clindamycin sulfoxide and minor metabolite N-desmethylclindamycin. Therefore, inhibitors of CYP3A4 and CYP3A5 may increase plasma concentrations of clindamycin and inducers of these isoenzymes may reduce plasma concentrations of clindamycin. In the presence of strong CYP3A4 inhibitors, monitor for adverse reactions. In the presence of strong CYP3A4 inducers such as rifampicin, monitor for loss of effectiveness.

In vitro studies indicate that clindamycin does not inhibit CYP1A2, CYP2C9, CYP2C19, CYP2E1 or CYP2D6 and only moderately inhibits CYP3A4.

Carcinogenesis, Mutagenesis, Impairment of Fertility

Long term studies in animals have not been performed with clindamycin to evaluate carcinogenic potential. Genotoxicity tests performed included a rat micronucleus test and an Ames Salmonella reversion test. Both tests were negative.

Fertility studies in rats treated orally with up to 300 mg/kg/day (approximately 1.1 times the highest recommended adult human dose based on mg/m^2) revealed no effects on fertility or mating ability.

Pregnancy:

Teratogenic effects

In clinical trials with pregnant women, the systemic administration of clindamycin during the second and third trimesters, has not been associated with an increased frequency of congenital abnormalities.

Clindamycin should be used during the first trimester of pregnancy only if clearly needed. There are no adequate and well-controlled studies in pregnant women during the first trimester of pregnancy. Because animal reproduction studies are not always predictive of the human response, this drug should be used during pregnancy only if clearly needed.

Reproduction studies performed in rats and mice using oral doses of clindamycin up to 600 mg/kg/day (2.1 and 1.1 times the highest recommended adult human dose based on mg/m^2, respectively) or subcutaneous doses of clindamycin up to 250 mg/kg/day (0.9 and 0.5 times the highest recommended adult human dose based on mg/m^2, respectively) revealed no evidence of teratogenicity.

CLEOCIN PHOSPHATE Sterile Solution contains benzyl alcohol. Benzyl alcohol can cross the placenta. See WARNINGS.

Nursing Mothers

Limited published data based on breast milk sampling reports that clindamycin appears in human breast milk in the range of less than 0.5 to 3.8 mcg/mL at dosages of 150 mg orally to 600 mg intravenously. Clindamycin has the potential to cause adverse effects on the breast-fed infant's gastrointestinal flora. If oral or intravenous clindamycin is required by a nursing mother, it is not a reason to discontinue breastfeeding, but an alternate drug may be preferred. Monitor the breast-fed infant for possible adverse effects on the gastrointestinal flora, such as diarrhea, candidiasis (thrush, diaper rash) or rarely, blood in the stool indicating possible antibacterial drug-associated colitis.

The developmental and health benefits of breastfeeding should be considered along with the mother's clinical need for clindamycin and any potential adverse effects on the breast-fed child from clindamycin or from the underlying maternal condition.

Pediatric Use

When CLEOCIN PHOSPHATE Sterile Solution is administered to the pediatric population (birth to 16 years) appropriate monitoring of organ system functions is desirable (see CLINICAL PHARMACOLOGY and DOSAGE AND ADMINISTRATION).

Usage in Newborns and Infants

This product contains benzyl alcohol as a preservative. Benzyl alcohol has been associated with a fatal "Gasping Syndrome" in premature infants. See WARNINGS.

The potential for the toxic effect in the pediatric population from chemicals that may leach from the single dose premixed IV preparation in plastic has not been evaluated. See WARNINGS.

Geriatric Use

Clinical studies of clindamycin did not include sufficient numbers of patients age 65 and over to determine whether they respond differently from younger patients. However, other reported clinical experience indicates that antibacterial drug-associated colitis and diarrhea (due to Clostridioides difficile) seen in association with most antibacterial drugs occur more frequently in the elderly (>60 years) and may be more severe. These patients should be carefully monitored for the development of diarrhea.

Pharmacokinetic studies with clindamycin have shown no clinically important differences between young and elderly subjects with normal hepatic function and normal (age-adjusted) renal function after oral or intravenous administration.

ADVERSE REACTIONS

The following reactions have been reported with the use of clindamycin.

Infections and Infestations: Clostridioides difficile colitis

Gastrointestinal: Antibacterial drug-associated colitis (see WARNINGS), pseudomembranous colitis, abdominal pain, nausea, and vomiting. The onset of pseudomembranous colitis symptoms may occur during or after antibacterial treatment (see WARNINGS). An unpleasant or metallic taste has been reported after intravenous administration of the higher doses of clindamycin phosphate.

Hypersensitivity Reactions: Maculopapular rash and urticaria have been observed during drug therapy. Generalized mild to moderate morbilliform-like skin rashes are the most frequently reported of all adverse reactions.

Severe skin reactions such as toxic epidermal necrolysis, some with fatal outcome, have been reported (see WARNINGS). Cases of acute generalized exanthematous pustulosis (AGEP), erythema multiforme, some resembling Stevens-Johnson syndrome, have been associated with clindamycin. Anaphylactic shock, anaphylactic reaction, hypersensitivity, and Kounis syndrome (acute myocardial ischemia with or without myocardial infarction may occur as part of an allergic reaction) have also been reported (see WARNINGS). Cutaneous vasculitis and symmetrical drug-related intertriginous and flexural exanthema have also been reported.

Skin and Mucous Membranes: Pruritus, vaginitis, angioedema and rare instances of exfoliative dermatitis have been reported (see Hypersensitivity Reactions).

Liver: Jaundice and abnormalities in liver function tests have been observed during clindamycin therapy.

Renal: Acute kidney injury (See WARNINGS).

Hematopoietic: Transient neutropenia (leukopenia) and eosinophilia have been reported. Reports of agranulocytosis and thrombocytopenia have been made. No direct etiologic relationship to concurrent clindamycin therapy could be made in any of the foregoing.

Immune System: Drug reaction with eosinophilia and systemic symptoms (DRESS) cases have been reported.

Local Reactions: Injection site irritation, pain, induration and sterile abscess have been reported after intramuscular injection and thrombophlebitis after intravenous infusion. Reactions can be minimized or avoided by giving deep intramuscular injections and avoiding prolonged use of indwelling intravenous catheters.

Musculoskeletal: Polyarthritis cases have been reported.

Cardiovascular: Cardiopulmonary arrest and hypotension have been reported following too rapid intravenous administration (see DOSAGE AND ADMINISTRATION).

OVERDOSAGE

Significant mortality was observed in mice at an intravenous dose of 855 mg/kg and in rats at an oral or subcutaneous dose of approximately 2618 mg/kg. In the mice, convulsions and depression were observed.

Hemodialysis and peritoneal dialysis are not effective in removing clindamycin from the serum.

DOSAGE AND ADMINISTRATION

If diarrhea occurs during therapy, this antibacterial drug should be discontinued (see WARNING box).

Clindamycin phosphate IM administration should be used undiluted.

Clindamycin phosphate IV administration should be diluted (see Dilution for IV use and IV infusion rates below).

Adults:

Parenteral (IM or IV Administration):

Serious infections due to aerobic gram-positive cocci and the more susceptible anaerobes (NOT generally including Bacteroides fragilis, Peptococcus species and Clostridium species other than Clostridium perfringens):

600–1200 mg/day in 2, 3 or 4 equal doses.

More severe infections, particularly those due to proven or suspected Bacteroides fragilis, Peptococcus species, or Clostridium species other than Clostridium perfringens:

1200–2700 mg/day in 2, 3 or 4 equal doses.

For more serious infections, these doses may have to be increased. In life-threatening situations due to either aerobes or anaerobes these doses may be increased. Doses of as much as 4800 mg daily have been given intravenously to adults. See Dilution for IV use and IV Infusion Rates section below.

Single intramuscular injections of greater than 600 mg are not recommended.

Alternatively, drug may be administered in the form of a single rapid infusion of the first dose followed by continuous IV infusion as follows:

Table 2: Serum Clindamycin Levels Maintained, Rapid Infusion Rate and Maintenance Infusion Rate
To maintain serum clindamycin levels | Rapid infusion rate | Maintenance infusion rate
Above 4 mcg/mL | 10 mg/min for 30 min | 0.75 mg/min
Above 5 mcg/mL | 15 mg/min for 30 min | 1.00 mg/min
Above 6 mcg/mL | 20 mg/min for 30 min | 1.25 mg/min

Pediatric Patients 1 month of age to 16 years:

Parenteral (IM or IV) Administration:

20 to 40 mg/kg/day in 3 or 4 equal doses. The higher doses would be used for more severe infections. Clindamycin should be dosed based on total body weight regardless of obesity. As an alternative to dosing on a body weight basis, pediatric patients may be dosed on the basis of square meters body surface: 350 mg/m^2/day for serious infections and 450 mg/m^2/day for more severe infections.

Parenteral therapy may be changed to oral CLEOCIN PEDIATRIC® Flavored Granules (clindamycin palmitate hydrochloride) or CLEOCIN HCl® Capsules (clindamycin hydrochloride) when the condition warrants and at the discretion of the physician.

In cases of β-hemolytic streptococcal infections, treatment should be continued for at least 10 days.

Pediatric Patients less than 1 month:

The recommended dosage is 15 to 20 mg/kg/day in 3 to 4 equal doses. See Table 3 regarding the dosing regimen for pediatric patients with post-menstrual age (PMA) less than or equal to 32 weeks, or greater than 32 weeks to less than or equal to 40 weeks.

Table 3: Dosing Regimens for Pediatric Patients with PMA less than or equal to 32 weeks, or greater than 32 weeks to less than or equal to 40 weeks
PMA (weeks) | Dose (mg/kg) | Dosing Interval (hours)
Less than or equal to 32 | 5 | 8
Greater than or equal to 32 to less than or equal to 40 | 7 | 8
PMA: Post-Menstrual age

Dilution for IV use and IV Infusion Rates:

The concentration of clindamycin in diluent for infusion should not exceed 18 mg per mL. Infusion rates should not exceed 30 mg per minute. The usual infusion dilutions and rates are as follows:

Dose | Diluent | Time
300 mg | 50 mL | 10 min
600 mg | 50 mL | 20 min
900 mg | 50–100 mL | 30 min
1200 mg | 100 mL | 40 min

Administration of more than 1200 mg in a single 1-hour infusion is not recommended.

Parenteral drug products should be inspected visually for particulate matter and discoloration prior to administration, whenever solution and container permit.

Dilution and Compatibility:

Physical and biological compatibility studies monitored for 24 hours at room temperature have demonstrated no inactivation or incompatibility with the use of CLEOCIN PHOSPHATE Sterile Solution (clindamycin phosphate) in IV solutions containing sodium chloride, glucose, calcium or potassium, and solutions containing vitamin B complex in concentrations usually used clinically. No incompatibility has been demonstrated with the antibacterial drugs cephalothin, kanamycin, gentamicin, penicillin or carbenicillin.

The following drugs are physically incompatible with clindamycin phosphate: ampicillin sodium, phenytoin sodium, barbiturates, aminophylline, calcium gluconate, and magnesium sulfate.

The compatibility and duration of stability of drug admixtures will vary depending on concentration and other conditions.

Physico-Chemical Stability of Diluted Solutions of CLEOCIN PHOSPHATE

Room Temperature:

6, 9 and 12 mg/mL (equivalent to clindamycin base) in dextrose injection 5%, sodium chloride injection 0.9%, or Lactated Ringers Injection in glass bottles or Mini-Bag containers, demonstrated physical and chemical stability for at least 16 days at 25°C. Also, 18 mg/mL (equivalent to clindamycin base) in dextrose injection 5%, in Mini-Bag containers, demonstrated physical and chemical stability for at least 16 days at 25°C.

Refrigeration:

6, 9 and 12 mg/mL (equivalent to clindamycin base) in dextrose injection 5%, sodium chloride injection 0.9%, or Lactated Ringers Injection in glass bottles or Mini-Bag containers, demonstrated physical and chemical stability for at least 32 days at 4°C.

IMPORTANT: This chemical stability information in no way indicates that it would be acceptable practice to use this product well after the preparation time. Good professional practice suggests that compounded admixtures should be administered as soon after preparation as is feasible.

Frozen:

6, 9 and 12 mg/mL (equivalent to clindamycin base) in dextrose injection 5%, sodium chloride injection 0.9%, or Lactated Ringers Injection in Mini-Bag containers demonstrated physical and chemical stability for at least eight weeks at -10°C.

Frozen solutions should be thawed at room temperature and not refrozen.

DIRECTIONS FOR DISPENSING

Pharmacy Bulk Package — Not for Direct Infusion

The Pharmacy Bulk Package is for use in a Pharmacy Admixture Service only under a laminar flow hood. Entry into the vial should be made with a small diameter sterile transfer set or other small diameter sterile dispensing device, and contents dispensed in aliquots using aseptic technique. Multiple entries with a needle and syringe are not recommended. AFTER ENTRY USE ENTIRE CONTENTS OF VIAL PROMPTLY. ANY UNUSED PORTION MUST BE DISCARDED WITHIN 24 HOURS AFTER INITIAL ENTRY.

DIRECTIONS FOR USE

CLEOCIN PHOSPHATE IV Solution in GALAXY Plastic Container

Premixed CLEOCIN PHOSPHATE IV Solution is for intravenous administration using sterile equipment. Check for minute leaks prior to use by squeezing bag firmly. If leaks are found, discard solution as sterility may be impaired. Do not add supplementary medication. Parenteral drug products should be inspected visually for particulate matter and discoloration prior to administration whenever solution and container permit. Do not use unless solution is clear and seal is intact.

Caution: Do not use plastic containers in series connections. Such use could result in air embolism due to residual air being drawn from the primary container before administration of the fluid from the secondary container is complete.

Preparation for Administration:

1. Suspend container from eyelet support.
2. Remove protector from outlet port at bottom of container.
3. Attach administration set. Refer to complete directions accompanying set.

Preparation of CLEOCIN PHOSPHATE in ADD-Vantage System

For IV Use Only. CLEOCIN PHOSPHATE 300 mg, 600 mg and 900 mg may be reconstituted in 50 mL (for 300 mg and 600 mg) or 100 mL (for 900 mg) of dextrose injection 5% or sodium chloride injection 0.9% in the ADD-diluent container. Refer to separate instructions for ADD-Vantage System.

HOW SUPPLIED

Each mL of CLEOCIN PHOSPHATE Sterile Solution contains clindamycin phosphate equivalent to 150 mg clindamycin, 0.5 mg disodium edetate, 9.45 mg benzyl alcohol added as preservative. When necessary, pH is adjusted with sodium hydroxide and/or hydrochloric acid. CLEOCIN PHOSPHATE is available in the following packages:

 | 25-2 mL vials | NDC 0009-0870-26
 | 25-4 mL vials | NDC 0009-0775-26
 | 25-6 mL vials | NDC 0009-0902-18
 | 5-60 mL Pharmacy Bulk Package | NDC 0009-0728-09

CLEOCIN PHOSPHATE is supplied in ADD-Vantage vials as follows:

NDC | Vial Size | Total Clindamycin Phosphate/vial
0009-6582-01 | 25-2 mL Vials | 300 mg
0009-3124-03 | 25-4 mL Vials | 600 mg
0009-3447-03 | 25-6 mL Vials | 900 mg

STORAGE AND HANDLING

Store at controlled room temperature 20° to 25°C (68° to 77°F) [see USP].

HOW SUPPLIED

CLEOCIN PHOSPHATE IV Solution in GALAXY plastic containers is a sterile solution of clindamycin phosphate with 5% dextrose. The single dose GALAXY plastic containers are available as follows:

24-300 mg/50 mL containers | NDC 0009-3381-02
24-600 mg/50 mL containers | NDC 0009-3375-02
24-900 mg/50 mL containers | NDC 0009-3382-02

STORAGE AND HANDLING

Exposure of pharmaceutical products to heat should be minimized. It is recommended that GALAXY plastic containers be stored at room temperature (25°C). Avoid temperatures above 30°C.

REFERENCES

1. Smith RB, Phillips JP: Evaluation of CLEOCIN HCl and CLEOCIN Phosphate in an Aged Population. Upjohn TR 8147-82-9122-021, December 1982.

ADD-Vantage® is a registered trademark of Hospira Inc.

CLEOCIN PHOSPHATE IV Solution in GALAXY plastic containers is manufactured for Pfizer Inc by Baxter Healthcare Corporation, Deerfield, IL 60015.

Galaxy and Mini-Bag are registered trademarks of Baxter International Inc.

This product's labeling may have been updated. For the most recent prescribing information, please visit www.pfizer.com.

LAB-0044-31.0
Revised: 10/2025

CLEOCIN PHOSPHATE® clindamycin sterile solution for injection, USP in ADD-Vantage® Vial

For Intravenous Use Only
NOT FOR INTRAMUSCULAR USE

INSTRUCTIONS FOR USE FOR ADD-VANTAGE SYSTEM—FOR IV USE ONLY

To Open Diluent Container:

Peel overwrap from the corner and remove container. Some opacity of the plastic due to moisture absorption during the sterilization process may be observed. This is normal and does not affect the solution quality or safety. The opacity will diminish gradually.

To Assemble Vial and Flexible Diluent Container:

(Use Aseptic Technique)

1. Remove the protective covers from the top of the vial and the vial port on the diluent container as follows:
  a. To remove the breakaway vial cap, swing the pull ring over the top of the vial and pull down far enough to start the opening (SEE FIGURE 1.), then pull straight up to remove the cap. (SEE FIGURE 2.) NOTE: Once the breakaway cap has been removed, DO NOT ACCESS VIAL WITH SYRINGE.
  b. To remove the vial port cover, grasp the tab on the pull ring, pull up to break the three tie strings, then pull back to remove the cover. (SEE FIGURE 3.)
2. Screw the vial into the vial port until it will go no farther. THE VIAL MUST BE SCREWED IN TIGHTLY TO ASSURE A SEAL. This occurs approximately 1/2 turn (180°) after the first audible click. (SEE FIGURE 4.) The clicking sound does not assure a seal; the vial must be turned as far as it will go. NOTE: Once the vial is seated, do not attempt to remove it. (SEE FIGURE 4.)
3. Recheck the vial to assure that it is tight by trying to turn it further in the direction of assembly.
4. Label appropriately.

To Prepare Admixture:

1. Squeeze the bottom of the diluent container gently to inflate the portion of the container surrounding the end of the drug vial.
2. With the other hand, push the drug vial down into the container telescoping the walls of the container. Grasp the inner cap of the vial through the walls of the container. (SEE FIGURE 5.)
3. Pull the inner cap from the drug vial. (SEE FIGURE 6.) Verify that the rubber stopper has been pulled out, allowing the drug and diluent to mix.
4. Mix container contents thoroughly and use within the specified time.

Preparation for Administration: (Use Aseptic Technique)

1. Confirm the activation and admixture of vial contents.
2. Check for leaks by squeezing container firmly. If leaks are found, discard unit as sterility may be impaired.
3. Close flow control clamp of administration set.
4. Remove cover from outlet port at bottom of container.
5. Insert piercing pin of administration set into port with a twisting motion until the pin is firmly seated. NOTE: See full directions on administration set carton.
6. Lift the free end of the hanger loop on the bottom of the vial, breaking the two tie strings. Bend the loop outward to lock it in the upright position, then suspend container from hanger.
7. Squeeze and release drip chamber to establish proper fluid level in chamber.
8. Open flow control clamp and clear air from set. Close clamp.
9. Attach set to venipuncture device. If device is not indwelling, prime and make venipuncture.
10. Regulate rate of administration with flow control clamp.

WARNING: Do not use flexible container in series connections.

ADD-Vantage® is a registered trademark of Hospira Inc.

LAB-0050-6.0
Revised March 2025

PRINCIPAL DISPLAY PANEL - 300 mg/2 mL Vial Label

2 mL Vial
NDC 0009-0870-21

Cleocin
Phosphate®
clindamycin injection, USP
300 mg/2 mL*
(150 mg/mL)

For intramuscular or intravenous use

Rx only

PRINCIPAL DISPLAY PANEL - 300 mg/2 mL Vial Carton

NDC 0009-0870-26
Contains 25 of NDC 0009-0870-21

25—2 mL Single Dose Vials

Cleocin Phosphate®
clindamycin injection, USP

300 mg/2 mL*

(150 mg/mL)

For intramuscular or intravenous use

Pfizer
Hospital

Rx only

PRINCIPAL DISPLAY PANEL - 600 mg/4 mL Vial Label

4 mL Vial
NDC 0009-0775-20

Cleocin Phosphate®
clindamycin injection, USP
600 mg/4 mL*
(150 mg/mL)

For intramuscular or intravenous use

Rx only

PRINCIPAL DISPLAY PANEL - 600 mg/4 mL Vial Carton

NDC 0009-0775-26
Contains 25 of NDC 0009-0775-20

25—4 mL Single Dose Vials

Cleocin Phosphate®
clindamycin injection, USP

600 mg/4 mL*

(150 mg/mL)

For intramuscular or intravenous use

Pfizer
Hospital

Rx only

PRINCIPAL DISPLAY PANEL - 900 mg/6 mL Vial Label

6 mL Vial
NDC 0009-0902-11

Cleocin Phosphate®
clindamycin injection, USP
900 mg/6 mL*
(150 mg/mL)

For intramuscular or intravenous use

Rx only

PRINCIPAL DISPLAY PANEL - 900 mg/6 mL Vial Carton

NDC 0009-0902-18
Contains 25 of NDC 0009-0902-11

25—6 mL Single Dose Vials

Cleocin Phosphate®
clindamycin injection, USP

900 mg/6 mL*

(150 mg/mL)

For intramuscular or intravenous use

Pfizer
Hospital

Rx only

PRINCIPAL DISPLAY PANEL - 9,000 mg/60 mL Vial Bulk Label

NDC 0009-0728-05

60 mL Pharmacy
Bulk Package

Cleocin
Phosphate®
clindamycin injection, USP
9,000 mg/60 mL*
(150 mg/mL)

For intramuscular or intravenous use
Not for direct infusion

Pfizer
Hospital

Rx only

Distributed by Pharmacia & Upjohn Company LLC
A subsidiary of Pfizer Inc., New York, NY 10001

PRINCIPAL DISPLAY PANEL - 9,000 mg/60 mL Vial Bulk Carton

NDC 0009-0728-09
Contains 5 of NDC 0009-0728-05

5—60 mL Pharmacy Bulk Packages

Cleocin Phosphate®
clindamycin injection, USP

9,000 mg/60 mL*

(150 mg/mL)

For intramuscular or intravenous use
Not for direct infusion

Pfizer
Hospital

Rx only

PRINCIPAL DISPLAY PANEL - 600 mg/4 mL Vial Label

NDC 0009-3124-01

Single Dose
4 mL ADD-Vantage™ Vial

Cleocin Phosphate®
clindamycin injection, USP
600 mg/4 mL*
(150 mg/mL)

For intravenous use only

Use only with the ADD-Vantage diluent container.

Pfizer Injectables

Rx only

PRINCIPAL DISPLAY PANEL - 600 mg/4 mL ADD-Vantage Vial Carton

25—4 mL Single Dose
ADD-Vantage® Vials

NDC 0009-3124-03
Contains 25 of NDC 0009-3124-01

Cleocin Phosphate®
clindamycin injection, USP

600 mg/4 mL*

(150 mg/mL)

For intravenous use only

Pfizer Injectables

Rx only

PRINCIPAL DISPLAY PANEL - 900 mg/6 mL Vial Label

NDC 0009-3447-01

Single Dose
6 mL ADD-Vantage™ Vial

Cleocin Phosphate®
clindamycin injection, USP
900 mg/6 mL*
(150 mg/mL)

For intravenous use only

Use only with the ADD-Vantage diluent container.

Pfizer Injectables

Rx only

PRINCIPAL DISPLAY PANEL - 900 mg/6 mL ADD-Vantage Vial Carton

25—6 mL Single Dose
ADD-Vantage® Vials

NDC 0009-3447-03
Contains 25 of NDC 0009-3447-01

Cleocin Phosphate®
clindamycin injection, USP

900 mg/6 mL*

(150 mg/mL)

For intravenous use only

Pfizer Injectables

Rx only

PRINCIPAL DISPLAY PANEL - 300 mg/ 50 mL Container Label

NDC 0009-3381-01

Cleocin Phosphate® IV Solution
clindamycin injection

300 mg/ 50 mL*
in 5% DEXTROSE
Rx only

For Intravenous Use

Code 2G3414
Sterile, Nonpyrogenic

GALAXY Single Dose Container

Recommended storage: Room temperature (25°C). Avoid temperatures above 30°C.
DOSAGE AND USE: See accompanying prescribing information.
Not for rapid injection or IV push.
Cautions: Do not add supplementary medication. Must not be used in series
connections. Check for minute leaks and solution clarity.
* Each 50 mL contains clindamycin phosphate equivalent to 300 mg clindamycin
and 2.5 g dextrose hydrous, USP with 2 mg edetate disodium dihydrate,
USP added. pH adjusted with sodium hydroxide and/or hydrochloric acid.
CLEOCIN PHOSPHATE is a registered trademark of
Pharmacia & Upjohn Company.
GALAXY is a registered trademark of Baxter International Inc.
Manufactured for Pfizer Inc by Baxter Healthcare
Corporation, Deerfield, IL 60015

Pfizer Injectables

Distributed by
Pharmacia & Upjohn Co
Division of Pfizer Inc
New York, NY 10017

PL 2501 Plastic
11152901
07-34-72-423

PRINCIPAL DISPLAY PANEL - 300 mg/ 50 mL Container Carton

2 x 12 x 50 mL Single Dose Containers
Contains 2 boxes of 12 of NDC 0009-3381-01

Cleocin Phosphate® IV Solution
clindamycin injection

Pfizer Injectables

300 mg/ 50 mL*
in 5% Dextrose
Rx only

NDC 0009-3381-02
Contains 24 of NDC 0009-3381-01
Code 2G3414

PRINCIPAL DISPLAY PANEL - 600 mg/ 50 mL Container Label

NDC 0009-3375-01

Cleocin Phosphate® IV Solution
clindamycin injection

600 mg/ 50 mL*
in 5% DEXTROSE
Rx only

For Intravenous Use

Code 2G3415
Sterile, Nonpyrogenic

GALAXY Single Dose Container

Recommended storage: Room temperature (25°C). Avoid temperatures above 30°C.
DOSAGE AND USE: See accompanying prescribing information.
Not for rapid injection or IV push.
Cautions: Do not add supplementary medication. Must not be used in series
connections. Check for minute leaks and solution clarity.
* Each 50 mL contains clindamycin phosphate equivalent to 600 mg clindamycin
and 2.5 g dextrose hydrous, USP with 2 mg edetate disodium dihydrate,
USP added. pH adjusted with sodium hydroxide and/or hydrochloric acid.
CLEOCIN PHOSPHATE is a registered trademark of
Pharmacia & Upjohn Company.
GALAXY is a registered trademark of Baxter International Inc.
Manufactured for Pfizer Inc by Baxter Healthcare Corporation,
Deerfield, IL 60015

Pfizer Injectables

Distributed by
Pharmacia & Upjohn Co
Division of Pfizer Inc
New York, NY 10017

PL 2501 Plastic
11153201
07-34-72-424

PRINCIPAL DISPLAY PANEL - 600 mg/ 50 mL Container Carton

2 x 12 x 50 mL Single Dose Containers
Contains 2 boxes of 12 of NDC 0009-3375-01

Cleocin Phosphate® IV Solution
clindamycin injection

Pfizer Injectables

600 mg/ 50 mL*
in 5% Dextrose
Rx only

NDC 0009-3375-02
Contains 24 of NDC 0009-3375-01
Code 2G3415

PRINCIPAL DISPLAY PANEL - 900 mg/ 50 mL Container Label

NDC 0009-3382-01

Cleocin Phosphate® IV Solution
clindamycin injection

900 mg/ 50 mL*
in 5% DEXTROSE
Rx only

For Intravenous Use

Code 2G3416
Sterile, Nonpyrogenic

GALAXY Single Dose Container

Recommended storage: Room temperature (25°C). Avoid temperatures above 30°C.
DOSAGE AND USE: See accompanying prescribing information.
Not for rapid injection or IV push.
Cautions: Do not add supplementary medication. Must not be used in series
connections. Check for minute leaks and solution clarity.
* Each 50 mL contains clindamycin phosphate equivalent to 900 mg clindamycin
and 2.5 g dextrose hydrous, USP with 2 mg edetate disodium dihydrate,
USP added. pH adjusted with sodium hydroxide and/or hydrochloric acid.
CLEOCIN PHOSPHATE is a registered trademark of
Pharmacia & Upjohn Company.
GALAXY is a registered trademark of Baxter International Inc.
Manufactured for Pfizer Inc by Baxter Healthcare Corporation,
Deerfield, IL 60015

Pfizer Injectables

Distributed by
Pharmacia & Upjohn Co
Division of Pfizer Inc
New York, NY 10017

PL 2501 Plastic
11153501
07-34-72-425

PRINCIPAL DISPLAY PANEL - 900 mg/ 50 mL Container Carton

2 x 12 x 50 mL Single Dose Containers
Contains 2 boxes of 12 of NDC 0009-3382-01

Cleocin Phosphate® IV Solution
clindamycin injection

Pfizer Injectables

900 mg/ 50 mL*
in 5% Dextrose
Rx only

NDC 0009-3382-02
Contains 24 of NDC 0009-3382-01
Code 2G3416

PRINCIPAL DISPLAY PANEL - 300 mg/2 mL ADD-vantage Vial Label

NDC 0009-6582-02

Single Dose
2 mL ADD-Vantage® Vial

Cleocin Phosphate®
clindamycin injection, USP
300 mg/2 mL*
(150 mg/mL)

For intravenous use only

Use only with the ADD-Vantage diluent container.

Pfizer Injectables

Rx only

PRINCIPAL DISPLAY PANEL - 300 mg/2 mL ADD-Vantage Vial Carton

25—2 mL Single Dose
ADD-Vantage® Vials

NDC 0009-6582-01
Contains 25 of NDC 0009-6582-02

Cleocin Phosphate®
clindamycin injection, USP

300 mg/2 mL*

(150 mg/mL)

For intravenous use only

Pfizer Injectables

Rx only